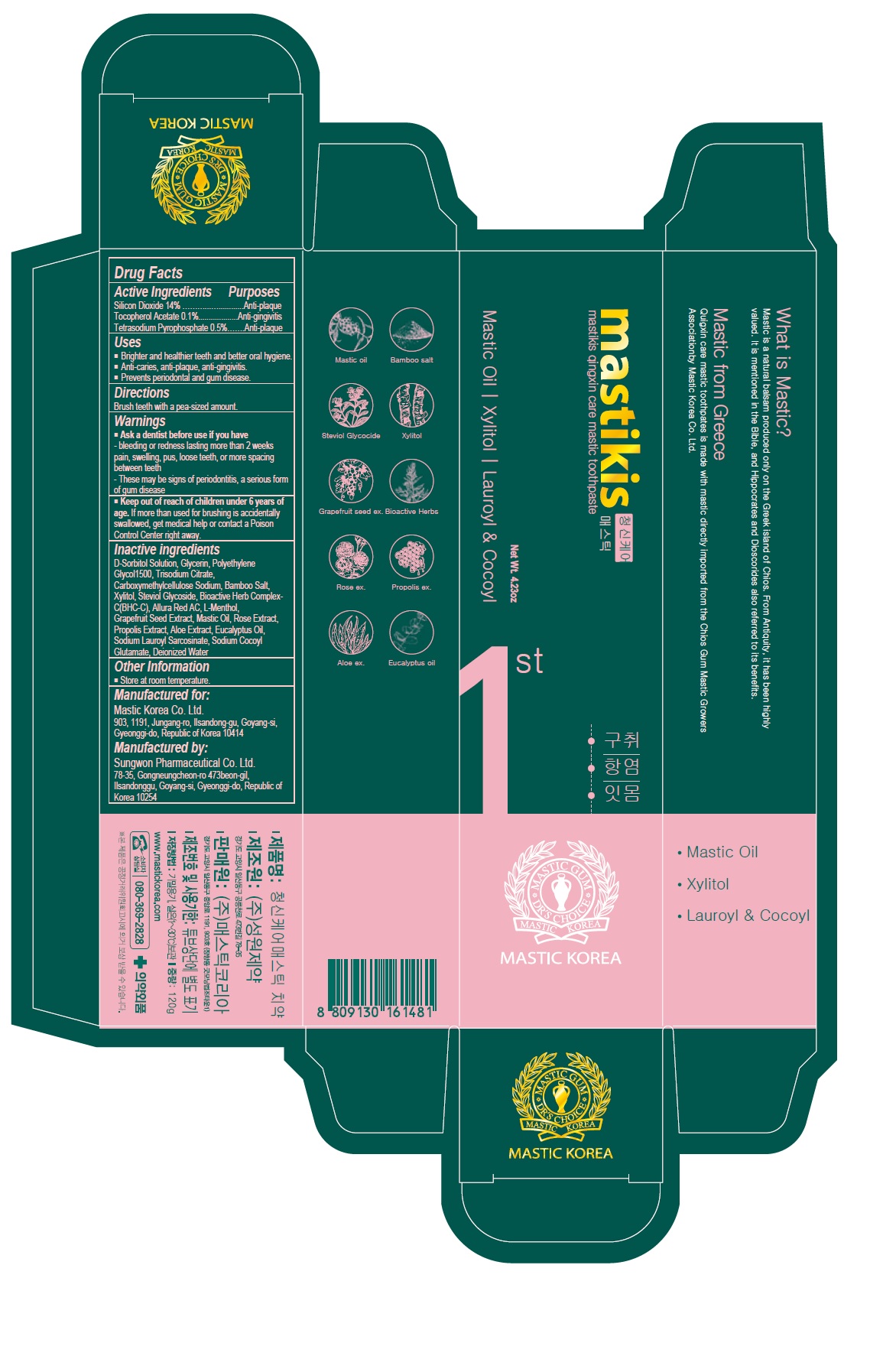 DRUG LABEL: Mastikis Qingxin Care Mastic
NDC: 79814-006 | Form: PASTE, DENTIFRICE
Manufacturer: Mastic Korea.Co.Ltd
Category: otc | Type: HUMAN OTC DRUG LABEL
Date: 20200921

ACTIVE INGREDIENTS: SILICON DIOXIDE 14 g/100 g; .ALPHA.-TOCOPHEROL ACETATE 0.1 g/100 g; SODIUM PYROPHOSPHATE 0.5 g/100 g
INACTIVE INGREDIENTS: SORBITOL; GLYCERIN; POLYETHYLENE GLYCOL 1600; SODIUM CITRATE, UNSPECIFIED FORM; CARBOXYMETHYLCELLULOSE SODIUM, UNSPECIFIED; XYLITOL; STEVIOSIDE; FD&C RED NO. 40; LEVOMENTHOL; CITRUS PARADISI SEED; PROPOLIS WAX; ALOE; EUCALYPTUS OIL; SODIUM LAUROYL SARCOSINATE; SODIUM COCOYL GLUTAMATE; WATER

79814-006_Mastikis Qingxin Care Mastic Toothpaste

ACTIVE INGREDIENT

Silicon Dioxide 14%

Tocopherel Acetate 0.1%

Tetrasodium Pyrophosphate 0.5%

INACTIVE INGREDIENT

D-Sorbitol Solution, Glycerin, Polyethylene Glycol1500, Trisodium Citrate, Carboxymethylcellulose Sodium, Bamboo salt, Xylitol, Steviol Glycoside, Bioactive Herb Complex-C(BHC-C), Allura Red AC, L-Menthol, Grapefruit Seed Extract, Mastic oil, Rose Extract, Propolis Extract, Aloe Extract, Eucalyptus Oil, Sodium Lauroyl Sarcosinate, Sodium Cocoyl Glutamate, Deionized Water

Keep out of Reach of Children.

PURPOSE

Anti-gingivitis

Anti-plaque

WARNINGS

Ask a dentist before use if you have

- bleeding or redness lasting more than 2 weeks pain, swelling, pus, losse teeth, or more spacing between teeth

- These may be signs of periodontitis, a serious form of gum disease

INDICATIONS AND USAGE

- Brighter and healthier teeth and better oral hygiene

- Anti-caries, anti-plaque, anti--gingivitis

- Prevents periodontal and gum disease

DOSAGE AND ADMINISTRATION

Brush teeth with a pea-sized amount